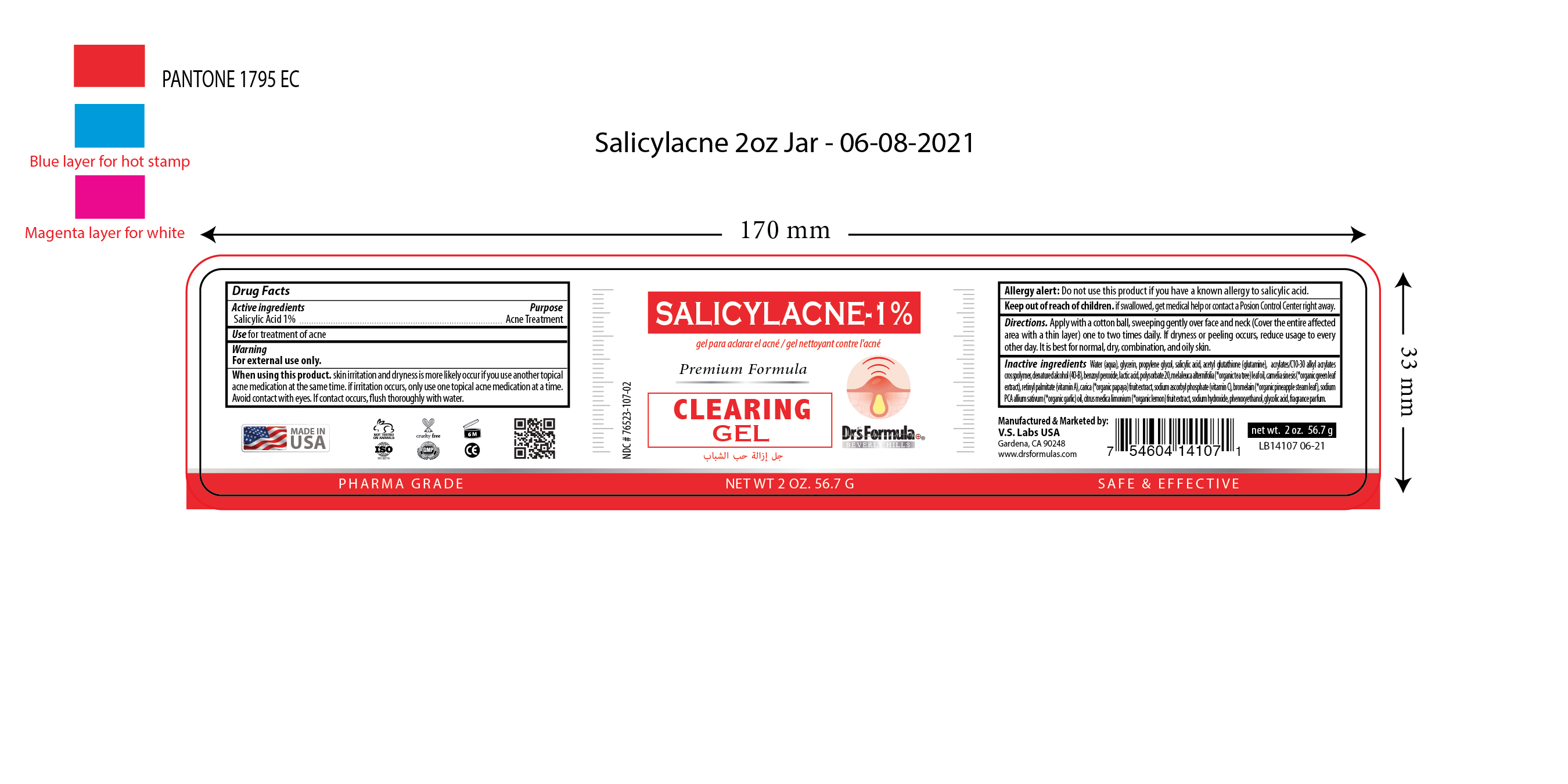 DRUG LABEL: Salicylacne-1% Clearing Gel
NDC: 76523-107 | Form: GEL
Manufacturer: Valley of the Sun Cosmetics
Category: otc | Type: HUMAN OTC DRUG LABEL
Date: 20210617

ACTIVE INGREDIENTS: SALICYLIC ACID 1 g/100 mL
INACTIVE INGREDIENTS: WATER; (2S)-3-PHENYLPROPANE-1,2-DIOL; ALLIUM SATIVUM WHOLE; GLYCERIN; BENZOYL PEROXIDE; POLYSORBATE 20; SODIUM ASCORBYL PHOSPHATE; GLYCOLIC ACID; SODIUM PIDOLATE; LACTIC ACID; GLUTAMINE; ACRYLATES CROSSPOLYMER-6; ALCOHOL; MELALEUCA ALTERNIFOLIA LEAF; GREEN TEA LEAF; VITAMIN A; CARICA PAPAYA WHOLE; STEM BROMELAIN; CITRUS MEDICA FRUIT; SODIUM HYDROXIDE; PHENOXYETHANOL; FRAGRANCE FLORAL ORC0902236

Salicylacne-1% Clearing Gel

Active Ingredients

Salicylic Acid 1%

Purpose

Acne Treatment

Uses

Use for treatment of acne

Warning

For external use only

Do not use

Allergy alert: Do not use this product if you have a known allergy to salicylic acid

When using this product

Skin irritation and dryness is more likely occur if you use another topical acne medication at the same time. If irritation occurs, only use one topical acne medication at a time. Avoid contact with eyes. If contact occurs, flush thoroughly with water.

Keep out of reach of children

If swallowed, get medical help or contact a Poison Control Center right away.

Directions

Apply with a cotton ball, sweeping gently over face and neck (Cover the entire affected area with a thin layer) one to two times daily. If dryness or peeling occurs, reduce usage to every other day. It is best for normal, dry, combination and oily skin.

Inactive ingredients

Water(aqua), Propylene glycol, Glycerin, Acetyl glutathione (glutamine), Acrylates/C10-30 alkyl acrylates crosspolymer, Denatured alcohol (40-B), Benzoyl peroxide, Lactic acid, Polysorbate 20, Melaleuca alternifolia (*organic tea tree) leaf oil, Camelia sinesis (*organic green tea)leaf extract, Retinyl Palmitate (vitamin A), Carica (*organic papaya) fruit extract, Sodium ascorbyl phosphate (vitamin C), Bromelain (*organic pineapple steam leaf), Sodium PCA, Allium sativum (*organic garlic) oil, Citrus medica limonium (*organic lemon) fruit extract), Sodium hydroxide, Phenoxyethanol, Glycolic acid, Fragrance parfum